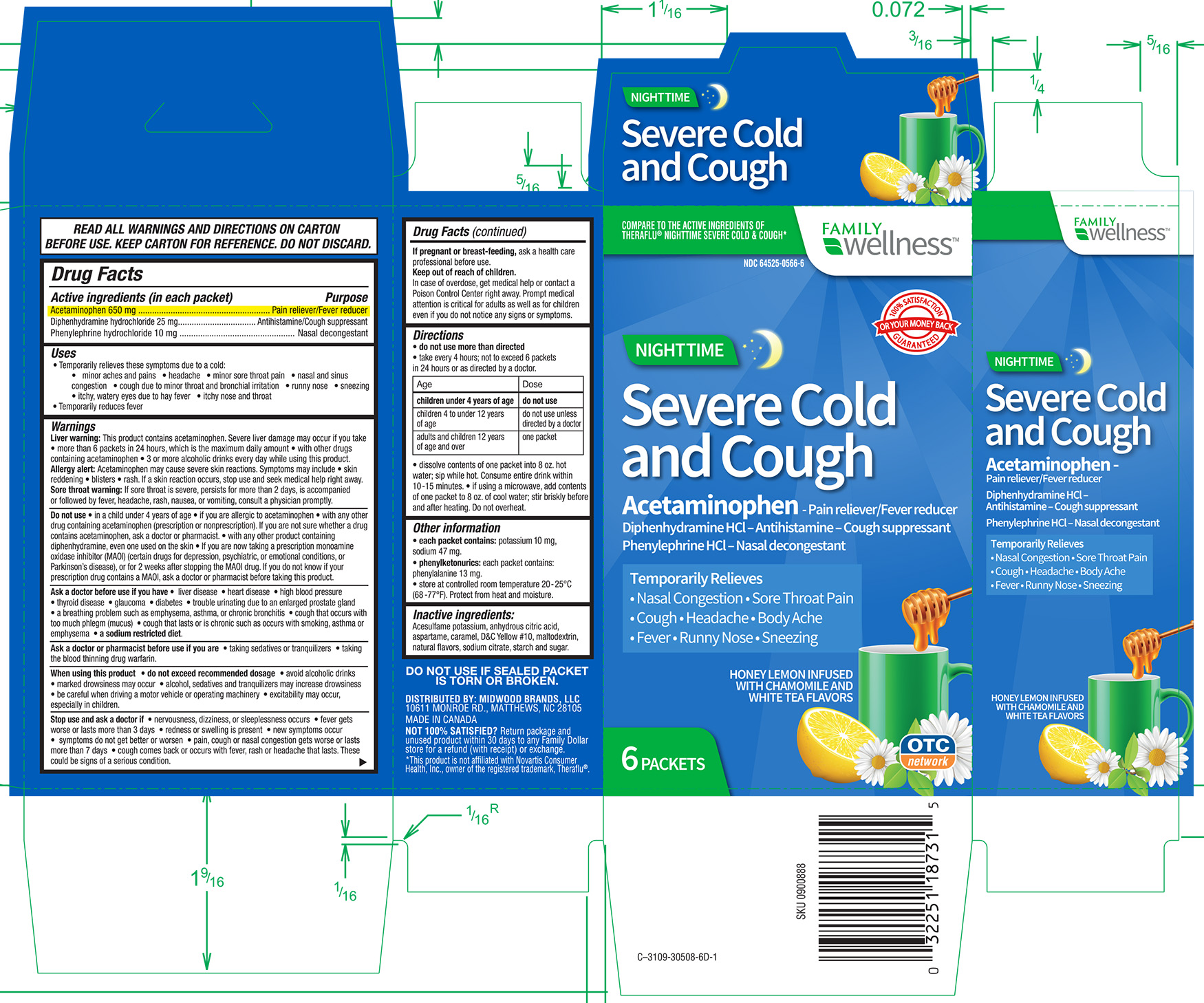 DRUG LABEL: Family Dollar Nighttime Severe Cold and Cough
NDC: 64525-0566 | Form: GRANULE, FOR SOLUTION
Manufacturer: Quality Home Products
Category: otc | Type: HUMAN OTC DRUG LABEL
Date: 20170519

ACTIVE INGREDIENTS: ACETAMINOPHEN 650 mg/1 1; DIPHENHYDRAMINE HYDROCHLORIDE 25 mg/1 1; PHENYLEPHRINE HYDROCHLORIDE 10 mg/1 1
INACTIVE INGREDIENTS: CITRIC ACID MONOHYDRATE; MALTODEXTRIN; SODIUM CITRATE; SUCROSE; ACESULFAME; ASPARTAME

Family Wellness Nighttime Severe Cold and Cough Honey lemon infused with Chamomile and White tea flavors

Active ingredients (in each packet) Purpose
Acetaminophen 650 mg ........................................Pain reliever/Fever reducer
Diphenhydramine hydrochloride 25 mg .........Anitihistamine/Cough suppressant
Phenylephrine hydrochloride 10 mg...................................Nasal decongestant.

Uses

- temporarily relieves these symptoms due to a cold:

- minor aches and pains - headache - minor sore throat pain

- nasal and sinus congestion - cough due to minor throat and bronchial irritation

- runny nose - sneezing - itchy, watery eyes due to hay fever

- itchy nose and throat

- temporarily reduces fever.

Warnings
Liver warning: This product contains acetaminophen. Severe liver damage may occur if you take - more than 6 packets in 24 hours, which is the maximum daily amount - with other drugs containing acetaminophen - 3 or more alcoholic drinks every day while using this product.

Allergy Alert: Acetaminophen may cause severe skin reactions. Symptoms may include - skin redenning - blisters - rash. If a skin reaction occurs, stop use and seek medical help right away.

Sore throat warning: If sore throat is severe, persists for more than 2 days, is accompanied or followed by fever, headache, rash, nausea, or vomiting, consult a doctor promptly.

Do not use:

- In a child under 4 years of age

- If you are allergic to acetaminophen
- with any other drug containing acetaminophen (prescription and nonprescription). If you are not sure whether a drug contains acetaminophen, ask a doctor or pharmacist.
- with any other product containing diphenhydramine, even one used on the skin
- If you are now taking a prescription monoamine oxidase (MAOI) (certain drugs for depression, psychiatric, or emotional conditions, or Parkinson's disease), or for 2 weeks after stopping the MAOI drug. If you do not know if your prescription drug contains a MAOI, ask a doctor or pharmacist before taking this product.

Ask a doctor before use if you have

- liver disease - heart disease - high blood pressure - thyroid disease - glaucoma - diabetes - trouble urinating due to an enlarged prostate gland - a breathing problem such as emphysema, asthma, or chronic bronchitis - cough that occurs with too much phlegm (mucus) - cough that lasts or is chronic such as occurs with smoking, asthma or emphysema.

- a sodium restricted diet.

Ask a doctor or pharmacist before use if you are:
- taking sedatives or tranquilizers
- taking the blood thinning drug warfarin.

When using this product:
- do not exceed recommended dosage
- avoid alcoholic drinks
- marked drowsiness may occur
- alcohol, sedatives and tranquilizers may increase drowsiness
- be careful when driving a motor vehicle or operating machinery
- excitability may occur, especially in children.

Stop use and ask a doctor if:

- nervousness, dizziness, or sleeplessness occurs
- fever gets worse or lasts more than 3 days
- redness or swelling is present
- new symptoms occur
- symptoms do not get better or worsen
- pain, cough or nasal congestion gets worse or lasts more than 7 days
- cough comes back or occurs with fever, rash or headache that lasts. These could be signs of a serious condition.

PREGNANCY OR BREAST FEEDING

If pregnant or breast-feeding, ask a health care professional before use.

Keep out of reach of children.

OVERDOSAGE

In case of overdose, get medical help or contact a Poison Control Center right away. Prompt medical attention is critical for adults as well as for children even if you do not notice any signs or symptoms.

Directions
- do not use more than directed
- take every 4 hours; not to exceed 6 packets in 24 hours or as directed by a doctor.

Age | Dose
children under 4 years of age | do not use
children 4 to under 12 years of age | do not use unless directed by a doctor
adults and children 12 years of age and over | one packet

- dissolve contents of one packet into 8 oz. hot water; sip while hot. Consume entire drink within 10-15 minutes.
- if using a microwave, add contents of one packet to 8 oz. of cool water: stir briskly before and after heating. Do not overheat.

Other information:
- each packet contains: potassium 10 mg, sodium 47 mg
- phenylketonurics: each packet contains phenylalanine 13 mg
- store at controlled room temperature 20-25C (68-77F). Protect from excessive heat and moisture.

INACTIVE INGREDIENT

Acesulfame potassium, anhydrous citric acid, Aspartame, Caramel Color, D and C Yellow 10, Maltodextrin, Natural Flavors, Sodium Citrate, Starch and Sugar.